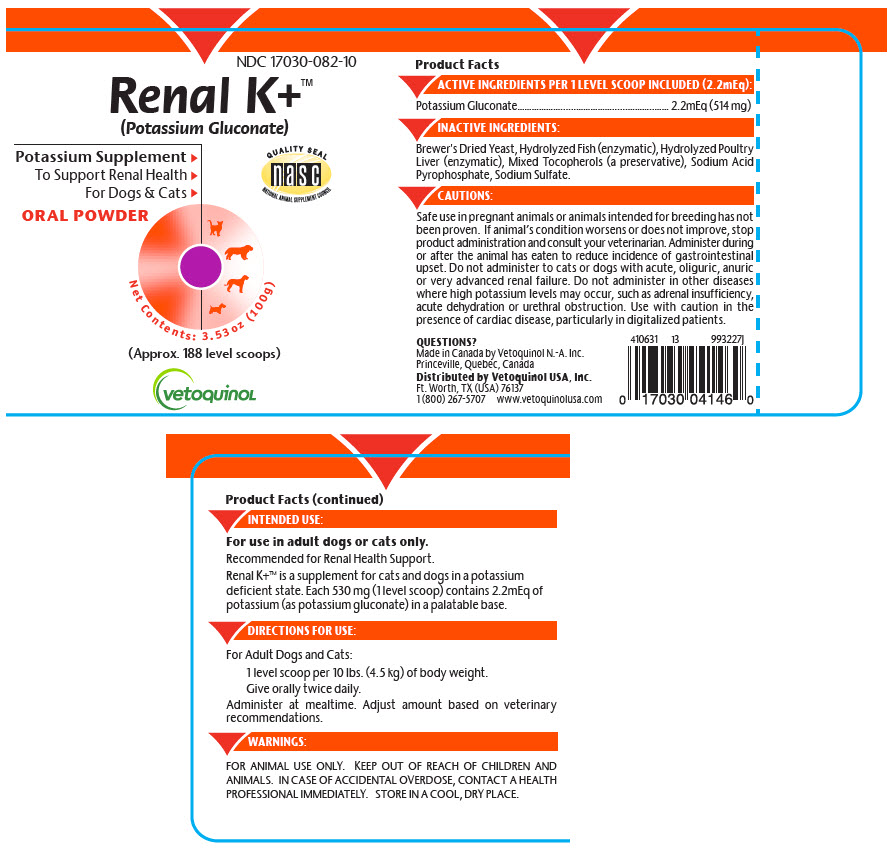 DRUG LABEL: Renal K Plus
NDC: 17030-082 | Form: POWDER
Manufacturer: Vetoquinol USA, Inc.
Category: animal | Type: OTC ANIMAL DRUG LABEL
Date: 20200219

ACTIVE INGREDIENTS: Potassium Gluconate 530 mg/0.0858 g
INACTIVE INGREDIENTS: SACCHAROMYCES CEREVISIAE; TOCOPHEROL; SODIUM ACID PYROPHOSPHATE; SODIUM SULFATE

Renal K+™

Product Facts

DESCRIPTION

ACTIVE INGREDIENTS PER 1 LEVEL SCOOP INCLUDED (2.2mEq):

Potassium Gluconate | 2.2mEq (514 mg)

INACTIVE INGREDIENTS:

Brewer's Dried Yeast, Hydrolyzed Fish (enzymatic), Hydrolyzed Poultry Liver (enzymatic), Mixed Tocopherols (a preservative), Sodium Acid Pyrophosphate, Sodium Sulfate.

CAUTIONS:

Safe use in pregnant animals or animals intended for breeding has not been proven. If animal's condition worsens or does not improve, stop product administration and consult your veterinarian. Administer during or after the animal has eaten to reduce incidence of gastrointestinal upset. Do not administer to cats or dogs with acute, oliguric, anuric or very advanced renal failure. Do not administer in other diseases where high potassium levels may occur, such as adrenal insufficiency, acute dehydration or urethral obstruction. Use with caution in the presence of cardiac disease, particularly in digitalized patients.

INTENDED USE:

For use in adult dogs or cats only.

Recommended for Renal Health Support.

Renal K+™ is a supplement for cats and dogs in a potassium deficient state. Each 530 mg (1 level scoop) contains 2.2mEq of potassium (as potassium gluconate) in a palatable base.

DIRECTIONS FOR USE:

For Adult Dogs and Cats:

1 level scoop per 10 lbs. (4.5 kg) of body weight.
Give orally twice daily.

Administer at mealtime. Adjust amount based on veterinary recommendations.

WARNINGS:

FOR ANIMAL USE ONLY. KEEP OUT OF REACH OF CHILDREN AND ANIMALS. IN CASE OF ACCIDENTAL OVERDOSE, CONTACT A HEALTH PROFESSIONAL IMMEDIATELY. STORE IN A COOL, DRY PLACE.

QUESTIONS?

Made in Canada by Vetoquinol N.-A. Inc.
Princeville, Quebec, Canada
Distributed by Vetoquinol USA, Inc.
Ft. Worth, TX (USA) 76137
1 (800) 267-5707
www.vetoquinolusa.com

410631
13
993227J

PRINCIPAL DISPLAY PANEL - 100 g Container Label

NDC 17030-082-10

Renal K+™
(Potassium Gluconate)

Potassium Supplement ▶
To Support Renal Health ▶
For Dogs & Cats ▶

ORAL POWDER

QUALITY SEAL
nasc
NATIONAL ANIMAL SUPPLEMENT COUNCIL

Net Contents: 3.53 oz (100g)

(Approx. 188 level scoops)

vetoquinol